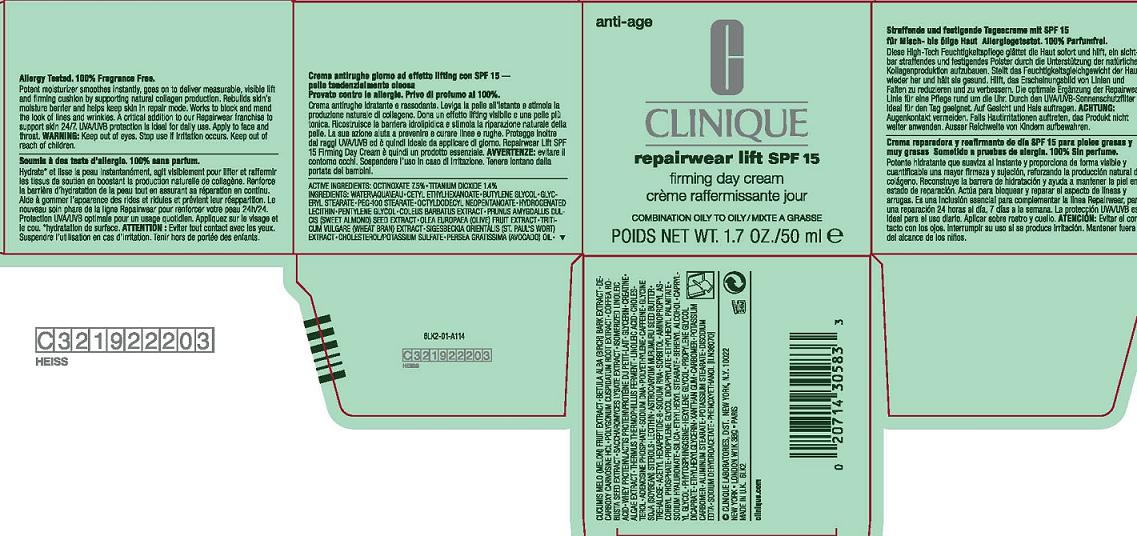 DRUG LABEL: REPAIRWEAR
NDC: 49527-009 | Form: CREAM
Manufacturer: CLINIQUE LABORATORIES INC
Category: otc | Type: HUMAN OTC DRUG LABEL
Date: 20110317

ACTIVE INGREDIENTS: OCTINOXATE 7.5 mL/100 mL; TITANIUM DIOXIDE 1.4 mL/100 mL
INACTIVE INGREDIENTS: WATER; BUTYLENE GLYCOL; GLYCERYL MONOSTEARATE; PROPYLENE GLYCOL MONOSTEARATE; GLYCERIN; HYDROGENATED SOYBEAN LECITHIN; PENTYLENE GLYCOL; OLIVE OIL; POTASSIUM SULFATE; CHOLESTEROL; AVOCADO OIL; CUCUMBER JUICE; POLYGONUM CUSPIDATUM ROOT; SACCHAROMYCES LYSATE; CREATINE; ADENOSINE PHOSPHATE; CAFFEINE; LECITHIN, SOYBEAN; ASTROCARYUM MURUMURU SEED BUTTER; TREHALOSE; SORBITOL; SILICON DIOXIDE; CAPRYLYL GLYCOL; HEXYLENE GLYCOL; XANTHAN GUM; CARBOMER HOMOPOLYMER TYPE C; EDETATE DISODIUM; PHENOXYETHANOL

ACTIVE INGREDIENT

active ingredients: octinoxate 7.50% [] titanium dioxide 1.40%

INACTIVE INGREDIENT

ingredients: water [] cetyl ethylhexanoate [] butylene glycol [] glyceryl stearate [] peg-100 stearate [] octyldodecyl neopentanoate [] hydrogenated lecithin [] pentylene glycol [] coleus barbatus extract [] prunus amygdalus dulcis (sweet almond) seed extract [] olea europaea (olive) fruit extract [] triticum vulgare (wheat bran) extract [] sigesbeckia orientalis extract [] cholesterol/potassium sulfate [] persea gratissima (avocado) oil [] cucumis melo (melon) fruit extract [] betula alba (birch) bark extract [] decarboxy carnosine hcl [] polygonum cuspidatum root extract [] coffea robusta seed extract [] saccharomyces lysate extract [] isomerized linoleic acid [] whey protein [] glycerin [] creatine [] algae extract [] thermus thermophillus ferment [] linoleic acid [] cholesterol [] adenosine phosphate [] sodium dna [] polyethylene [] caffeine [] glycine soja (soybean) sterols [] lecithin [] astrocaryum murumuru seed butter [] trehalose [] acetyl hexapeptide-8 [] sodium rna [] sorbitol [] aminopropyl ascorbyl phosphate [] propylene glycol dicaprylate [] ethylhexyl palmitate [] sodium hyaluronate [] silica [] ethylhexyl stearate [] behenyl alcohol [] caprylyl glycol [] phytosphingosine [] hexylene glycol [] propylene glycol dicaprate [] ethylhexylglycerin [] xanthan gum [] carbomer [] potassium carbomer [] aluminum stearate [] potassium stearate [] disodium edta [] sodium dehydroacetate [] phenoxyethanol

WARNINGS

warning: keep out of eyes. stop use if irritation occurs

keep out of reach of children

PACKAGE LABEL

PRINCIPAL DISPLAY PANEL

CLINIQUE

REPAIRWEAR LIFT SPF 15

FIRMING CREAM

OILY/COMB SKIN

NT WT 1.7 OZ./50 ML

clinique laboratories distr.

new york, ny 10022